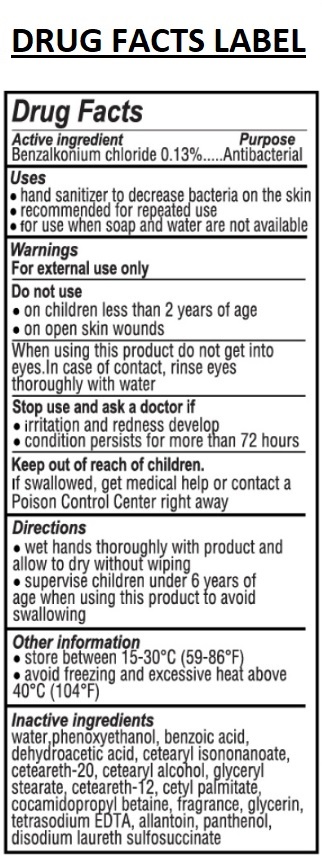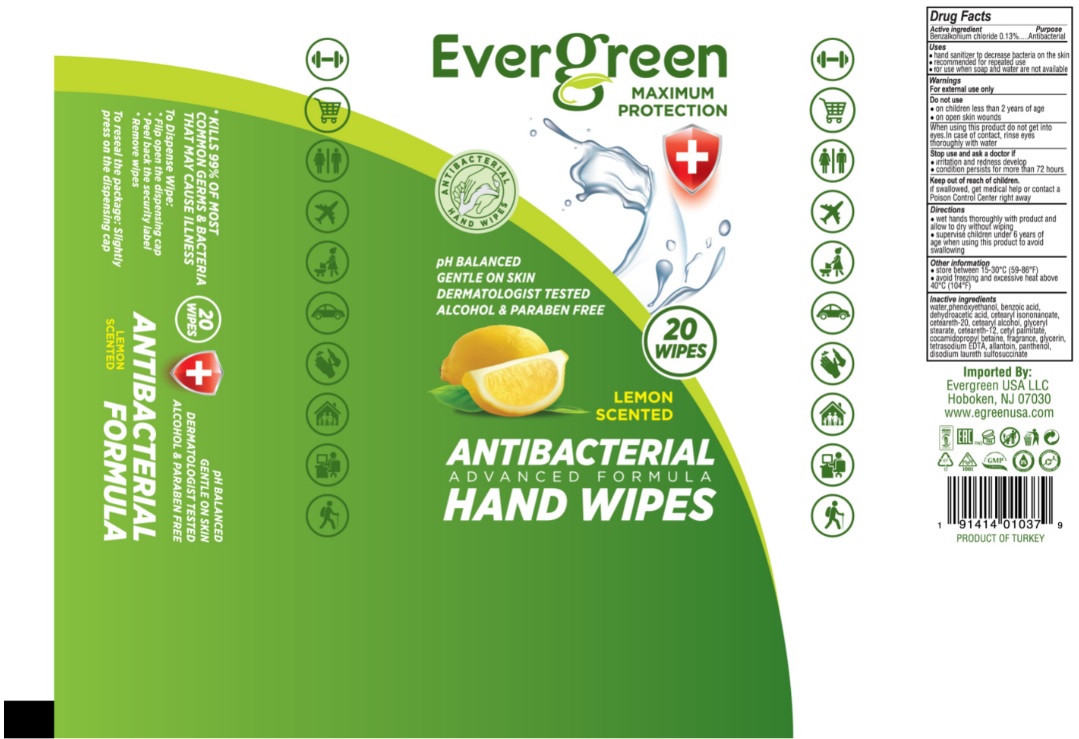 DRUG LABEL: Evergreen
NDC: 79881-020 | Form: CLOTH
Manufacturer: ELA KOZMETIK VE HIJYENIK URUNLERI SANAYI TICARET LIMITED SIRKETI
Category: otc | Type: HUMAN OTC DRUG LABEL
Date: 20200811

ACTIVE INGREDIENTS: BENZALKONIUM CHLORIDE 0.13 g/100 g
INACTIVE INGREDIENTS: WATER; PHENOXYETHANOL; BENZOIC ACID; DEHYDROACETIC ACID; CETEARYL ISONONANOATE; POLYOXYL 20 CETOSTEARYL ETHER; CETOSTEARYL ALCOHOL; GLYCERYL MONOSTEARATE; CETEARETH-12; CETYL PALMITATE; COCAMIDOPROPYL BETAINE; GLYCERIN; EDETATE SODIUM; ALLANTOIN; PANTHENOL; DISODIUM LAURETH SULFOSUCCINATE

Evergreen ANTIBACTERIAL ADVANCED FORMULA HAND WIPES

Active ingredient

Benzalkonium chloride 0.13%

Purpose

Antibacterial

Uses

• hand sanitizer to decrease bacteria on the skin

• recommended for repeated use

• for use when soap and water are not available

Warnings

For external use only

Do not use

• on children less than 2 years of age

• on open skin wounds

When using this product do not get into eyes. In case of contact, rinse eyes thoroughly with water

Stop use and ask a doctor if

• irritation and redness develop

• condition persists for more than 72 hours

Keep out of reach of children.

If swallowed, get medical help or contact a Poison Control Center right away

Directions

• wet hands thoroughly with product and allow to dry without wiping

• supervise children under 6 years of age when using this product to avoid swallowing

Other information

• store between 15-30°C (59-86°F)

• avoid freezing and excessive heat above 40°C (104°F)

Inactive ingredients

water, phenoxyethanol, benzoic acid, dehydroacetic acid, cetearyl isononanoate, ceteareth-20, cetearyl alcohol, glyceryl stearate, ceteareth-12, cetyl palmitate, cocamidopropyl betaine, fragrance, glycerin, tetrasodium EDTA, allantoin, panthenol, disodium laureth sulfosuccinate

MAXIMUM PROTECTION

LEMON SCENTED

pH BALANCED

GENTLE ON SKIN

DERMATOLOGIST TESTED

ALCOHOL & PARABEN FREE

*KILLS 99% OF MOST COMMON GERMS & BACTERIA THAT MAY CAUSE ILLNESS

To Dispense Wipe:

* Flip open the dispensing cap

* Peel back the security label

* Remove wipes

To reseal the package: Slightly press on the dispensing cap

Imported By:

Evergreen USA LLC

Hoboken, NJ 07030

www.egreenusa.com

PRODUCT OF TURKEY